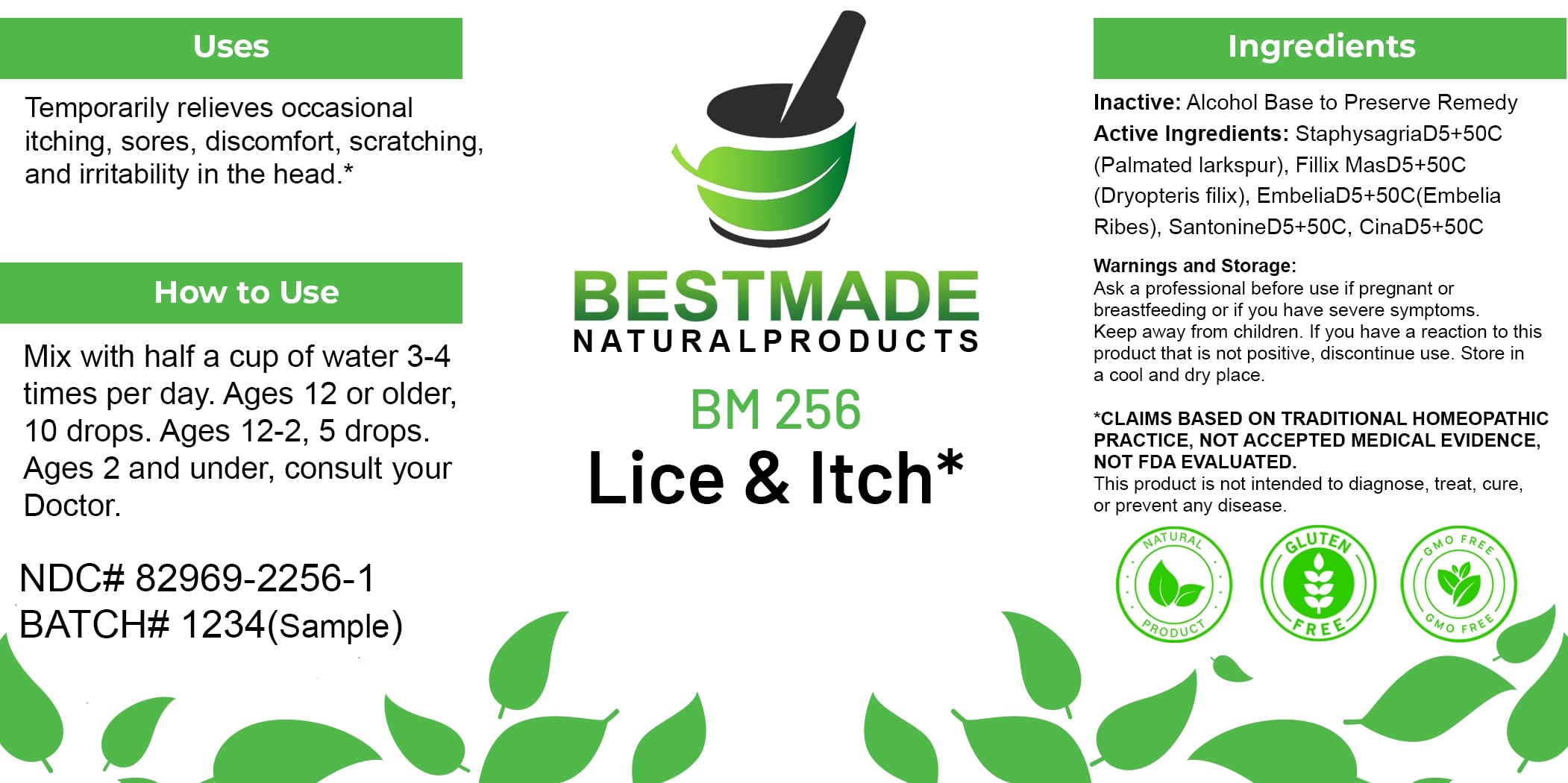 DRUG LABEL: Bestmade Natural Products BM256
NDC: 82969-2256 | Form: LIQUID
Manufacturer: Bestmade Natural Products
Category: homeopathic | Type: HUMAN OTC DRUG LABEL
Date: 20250306

ACTIVE INGREDIENTS: DRYOPTERIS FILIX-MAS ROOT 30 [hp_C]/30 [hp_C]; SANTONIN 30 [hp_C]/30 [hp_C]; ARTEMISIA CINA FLOWER 30 [hp_C]/30 [hp_C]; DELPHINIUM STAPHISAGRIA SEED 30 [hp_C]/30 [hp_C]; EMBELIA RIBES WHOLE 30 [hp_C]/30 [hp_C]
INACTIVE INGREDIENTS: ALCOHOL 30 [hp_C]/30 [hp_C]

BM256

DOSAGE AND ADMINISTRATION

How to Use

Mix with half a cup of water 3-4 times per day. Ages 12 or older, 10 drops. Ages 12-2, 5 drops. Ages 2 and under, consult your Doctor.

INACTIVE INGREDIENT

Ingredients

Inactive: Alcohol Base to Preserve Remedy

ACTIVE INGREDIENT

Active Ingredients: Staphysagria D5+50C (Palmated larkspur), Filix Mas D5+50C (Dryopteris filix), Embelia D5+50C (Embelia Ribes), Santonine D5+50C, Cina D5+50C

Uses

Temporarily relieves occasional itching, sores, discomfort, scratching, and irritability in the head.*

*CLAIMS BASED ON TRADITIONAL HOMEOPATHIC PRACTICE, NOT ACCEPTED MEDICAL EVIDENCE, NOT FDA EVALUATED.

This product is not intended to diagnose, treat, cure, or prevent any disease.

Uses

Temporarily relieves occasional itching, sores, discomfort, scratching, and irritability in the head.*

*CLAIMS BASED ON TRADITIONAL HOMEOPATHIC PRACTICE, NOT ACCEPTED MEDICAL EVIDENCE, NOT FDA EVALUATED.

This product is not intended to diagnose, treat, cure, or prevent any disease.

KEEP OUT OF REACH OF CHILDREN

Warnings and Storage:

Ask a professional before use if pregnant or breastfeeding or if you have severe symptoms. Keep away from children. If you have a reaction to this product that is not positive, discontinue use. Store in a cool and dry place.

Warnings and Storage:

Ask a professional before use if pregnant or breastfeeding or if you have severe symptoms. Keep away from children. If you have a reaction to this product that is not positive, discontinue use. Store in a cool and dry place.

*CLAIMS BASED ON TRADITIONAL HOMEOPATHIC PRACTICE, NOT ACCEPTED MEDICAL EVIDENCE, NOT FDA EVALUATED.

This product is not intended to diagnose, treat, cure, or prevent any disease.

Entire package label